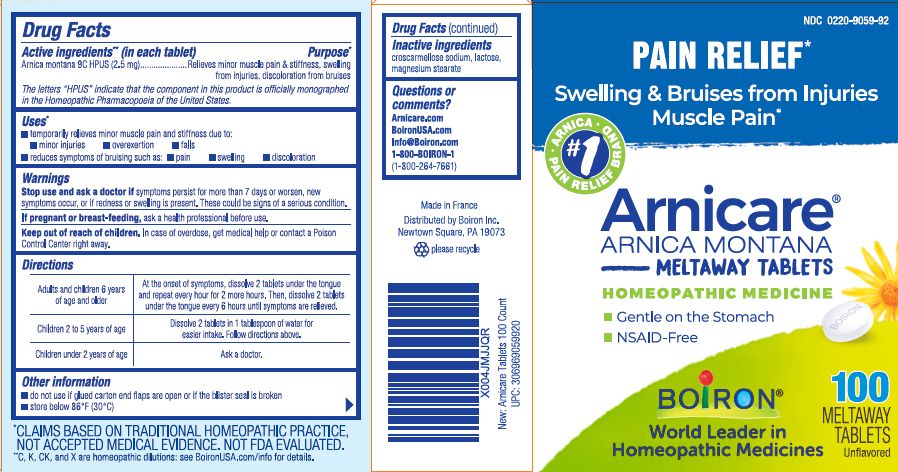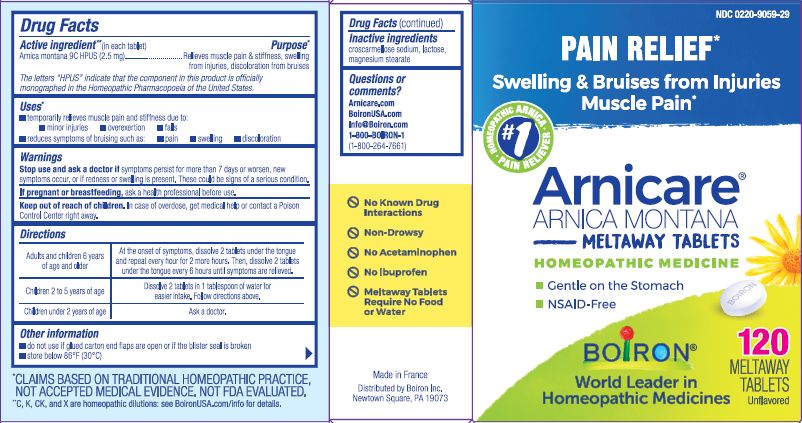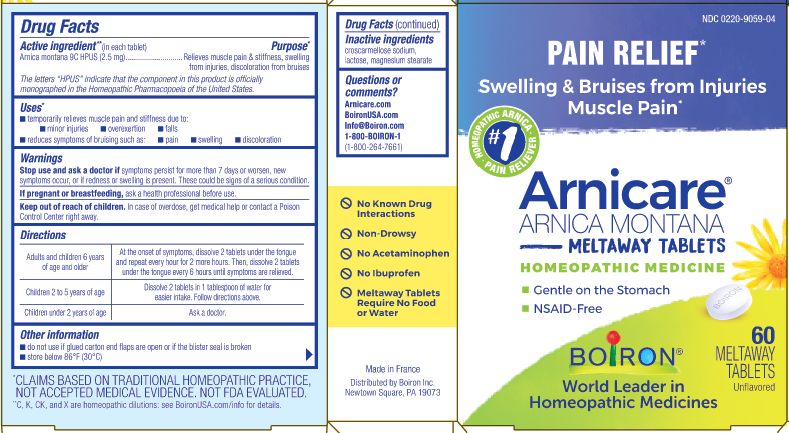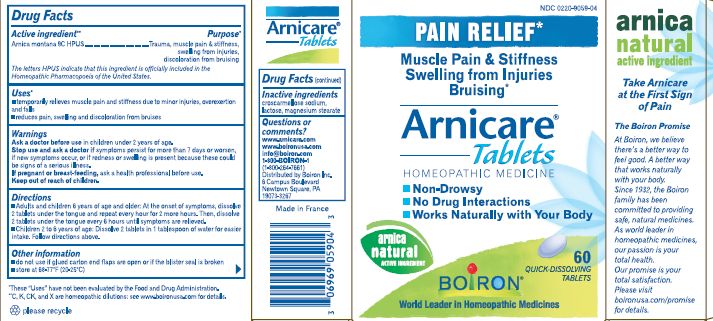 DRUG LABEL: Arnicare Arnica
NDC: 0220-9059 | Form: TABLET
Manufacturer: Laboratoires Boiron
Category: homeopathic | Type: HUMAN OTC DRUG LABEL
Date: 20250320

ACTIVE INGREDIENTS: ARNICA MONTANA 9 [hp_C]/1 1
INACTIVE INGREDIENTS: CROSCARMELLOSE SODIUM; LACTOSE; MAGNESIUM STEARATE

Arnicare Tablets

Active ingredient** (in each tablet)

Arnica Montana 9C HPUS (2.5 mg)

The letters "HPUS" indicate that the component in this product is officially monographed in the Homeopathic Pharmacopoeia of the United States.

Purpose*

Arnica montana 9C HPUS (2.5 mg) ... Relieves minor muscle pain & stiffness, swelling from injuries, discoloration from bruises

Uses*

temporarily relieves minor muscle pain and stiffness due to:

- minor injuries
- overexertion
- falls
- reduces symptoms of bruising such as:
- pain
- swelling
- discoloration

Stop use and ask a doctor if symptoms persist for more than 7 days or worsen, new symptoms occur, or if redness or swelling is present. These could be signs of a serious condition.

PREGNANCY OR BREAST FEEDING

If pregnant or breast-feeding, ask a health professional before use.

Keep out of reach of children. In case of overdose, get medical help or contact a Poison Control Center right away.

Directions

Adults and children 6 years of age or older - At the onset of symptoms, dissolve 2 tablets under the tongue and repeat every hour for 2 more hours. Then, dissolve 2 tablets under the tongue every 6 hours until symptoms are relieved.

Children 2 to 5 years of age - Dissolve 2 tablets in 1 tablespoon for easier intake. Follow directions above.

Children under 2 years of age - Ask a doctor.

INACTIVE INGREDIENT

croscarmellose sodium, lactose, magnesium, stearate

- do not use if glued carton end flaps are open or if the blister seal is broken
- store below 86°F (30°C)

No known drug interactions

Pain Relief*

Swelling & Bruise from Injuries Muscle Pain*

Gentle on the Stomach

NSAID-Free

60 Meltaway Tablets unflavored

100 Meltawat Tablets unflavored

120 Meltaway Tablets unflavored

*CLAIMS BASED ON TRADITIONAL HOMEOPATHIC PRACTICE NOT ACCEPTED MEDICAL EVIDENCE. NOT FDA EVALUATED.
**C,K,CK, and X are homeopathic dilutions: see BoironUSA.com/info for details.

Questions or Comments?

Arnicare.com

BoironUSA.com

Info@Boiron.com

1-800-BOIRON-1
(1-800-264-7661)
Distributed by Boiron, Inc.

Newtown Square, PA 19073

Made in France